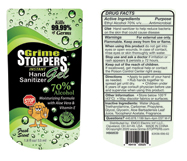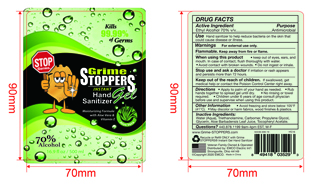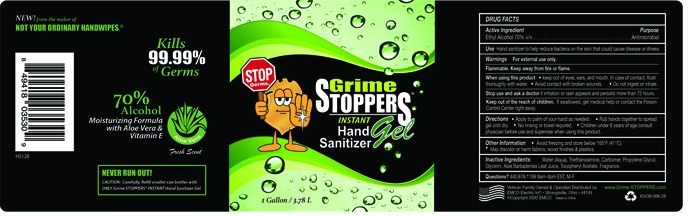 DRUG LABEL: Grime STOPPERS Instant Hand Sanitizer
NDC: 63436-006 | Form: GEL
Manufacturer: EMCO Electric International
Category: otc | Type: HUMAN OTC DRUG LABEL
Date: 20210218

ACTIVE INGREDIENTS: ALCOHOL 70 mL/100 mL
INACTIVE INGREDIENTS: GLYCERIN 0.2 mL/100 mL; .ALPHA.-TOCOPHEROL ACETATE 0.001 mL/100 mL; PROPYLENE GLYCOL 0.1 mL/100 mL; WATER 29.18 mL/100 mL; ALOE VERA LEAF 0.001 mL/100 mL; TROLAMINE 0.26 mL/100 mL; CARBOMER HOMOPOLYMER, UNSPECIFIED TYPE 0.26 mL/100 mL

Hand Sanitizer

ACTIVE INGREDIENT(S)

Ethyl Alcohol 70% v/v

PURPOSE

Anitmicrobial

DOSAGE & ADMINISTRATION

Topical Gel applied to outer surface of the body, specifically hands.

USE

Gel hand sanitizer to help reduce bacteria on the skin that could cause disease or illness. Repeat use as needed.

WARNINGS

- For external use only.
- Flammable. Keep away from fire or flame.

When using this product

- Keep out of eyes, ears, and mouth. In case of contact, flush thoroughly with water.
- Avoid contact with broken wounds.
- Do not ingest or inhale.

Stop use and ask a doctor

if irritation or rash appears and persists more than 72 hours.

Keep out of the reach of children.

- If swallowed, get medical help or contact the Poison Control Center right away.

DIRECTIONS

- Apply to palm of your hand as needed.
- Rub hands together to spread gel until dry.
- No rinsing or towel required.
- Children under 6 years of age consult physcian before use and supervise when using this product.

OTHER INFORMATION

- Avoid freezing and store below 105°F (41°C)
- May discolor or harm fabrics, wood finishes and plastics.

INACTIVE INGREDIENTS

- Water
- Triethanolamine
- Carbomer
- Propylene Glycol
- Glycerin
- Aloe Barbadensis Leaf Juice
- Tocopheryl Acetate

Grime STOPPERS Instant Hand Sanitizer Gel

53mL NDC: 63436-006-02

500ml NDC: 63436-006-16

3.78mL NDC: 63436-006-28